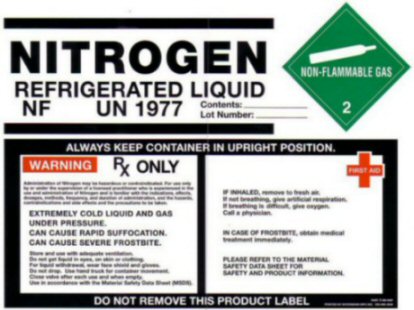 DRUG LABEL: NITROGEN
NDC: 52698-002 | Form: GAS
Manufacturer: Bill Munn Supply Inc, dba Munn Supply
Category: prescription | Type: HUMAN PRESCRIPTION DRUG LABEL
Date: 20100101

ACTIVE INGREDIENTS: NITROGEN 99 L/100 L

NITROGEN REFRIGERATED LIQUID NF UN 1977 NON-FLAMMABLE GAS CONTENTS ________________ LOT NUMBER ________________ ALWAYS KEEP CONTAINER IN UPRIGHT POSITION DO NOT REMOVE THIS PRODUCT LABEL WARNING Rx ONLY. PLEASE REFER TO THE MATERIAL SAFETY DATA SHEET FOR SAFETY AND PRODUCT INFORMATION
IF INHALED, REMOVE TO FRESH AIR. IF NOT BREATHING, GIVE ARTIFICIAL RESPIRATION. IF BREATHING IS DIFFICULT, GIVE OXYGEN. CALL A PHYSICIAN. IN CASE OF FROSTBITE, OBTAIN MEDICAL TREATMENT IMMEDIATELY.
PART # DB-NNF PRINTED BY RATERMANN MFG INC. 925-606-2949

GENERAL WARNINGS AND PRECAUTIONS

ADMINISTRATION OF NITROGEN MAY BE HAZARDOUS OR CONTRAINDICATED. FOR USE ONLY BY OR UNDER THE SUPERVISION OF A LICENSED PRACTITIONER WHO IS EXPERIENCED IN THE USE AND ADMINISTRATION OF NITROGEN AND IS FAMILIAR WITH THE INDICATIONS, EFFECTS, DOSAGES, METHODS, FREQUENCY, AND DURATION OF ADMINISTRATION, AND THE HAZARDS CONTRAINDICATIONS AND SIDE EFFECTS AND THE PRECAUTIONS TO BE TAKEN.
EXTREMELY COLD LIQUID AND GAS UNDER PRESSURE. CAN CAUSE RAPID SUFFOCATION. CAN CAUSE SEVERE FROSTBITE. STORE AND USE WITH ADEQUATE VENTILATION. DO NOT GET LIQUID IN EYES ON SKIN OR CLOTHING. FOR LIQUID WITHDRAWAL, WEAR FACE SHIELD AND GLOVES. DO NOT DROP. USE HAND TRUCK FOR CONTAINER MOVEMENT. CLOSE VALVE AFTER EACH USE AND WHEN EMPTY. USE IN ACCORDANCE WITH THE MATERIAL SAFETY DATA SHEET (MSDS).